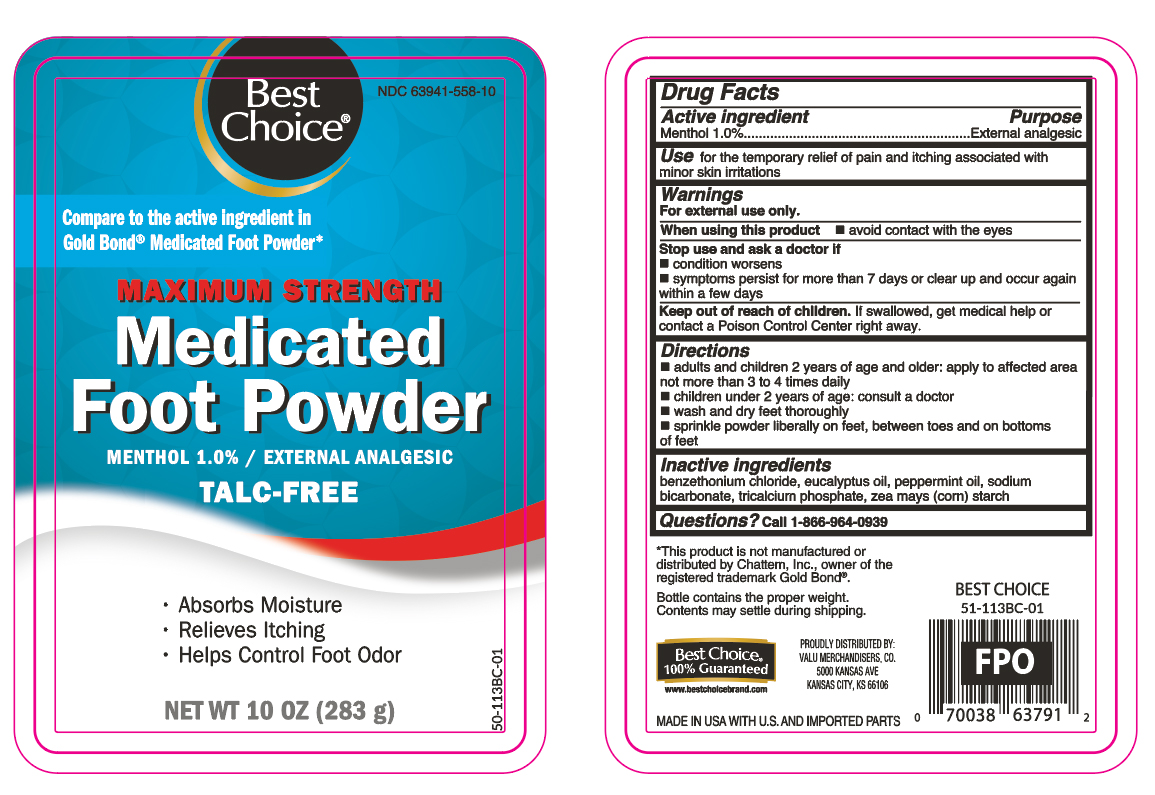 DRUG LABEL: Menthol
NDC: 63941-558 | Form: POWDER
Manufacturer: VALU MERCHANDISERS, CO
Category: otc | Type: HUMAN OTC DRUG LABEL
Date: 20251124

ACTIVE INGREDIENTS: MENTHOL 2.8 g/283 g
INACTIVE INGREDIENTS: STARCH, CORN; PEPPERMINT OIL; SODIUM BICARBONATE; TRICALCIUM PHOSPHATE; EUCALYPTUS OIL; BENZETHONIUM CHLORIDE

Medicated Foot Powder -Talc Free

Active ingredient

Menthol 1.0%

Purpose

External analgesic

Use

for the temporary relief of pain and itching associated with minor skin irritations

Warnings

For external use only.

When using this product

- avoid contact with the eyes

Stop use and ask a doctor if

- conditions worsens
- symptoms persists for more than 7 days or clear up and occur again within a few days

Keep out of reach of children.

If swallowed, get medical help or contact a Poison Control Center right away.

Directions

- adults and children 2 years of age and older: apply to affected area not more than 3 to 4 times daily
- children under 2 years of age: consult a doctor
- wash and dry feet thoroughly
- sprinkle powder liberally on feet, between toes and on bottoms of feet

Inactive ingredients

benzethonium chloride, eucalyptus oil, peppermint oil, sodium bicarbonate, tricalcium phosphate, zea mays (corn) starch

Questions?

Call 1-866-964-0939

Principal Display Panel

Best Choice

MAXIMUM STRENGTH

Medicated Foot Powder

MENTHOL 1.0% / EXTERNAL ANALGESIC

TALC-FREE

- Absorbs Moisture
- Relieves Itching
- Helps Control Foot Odor

NET WT 10 oz (283g)